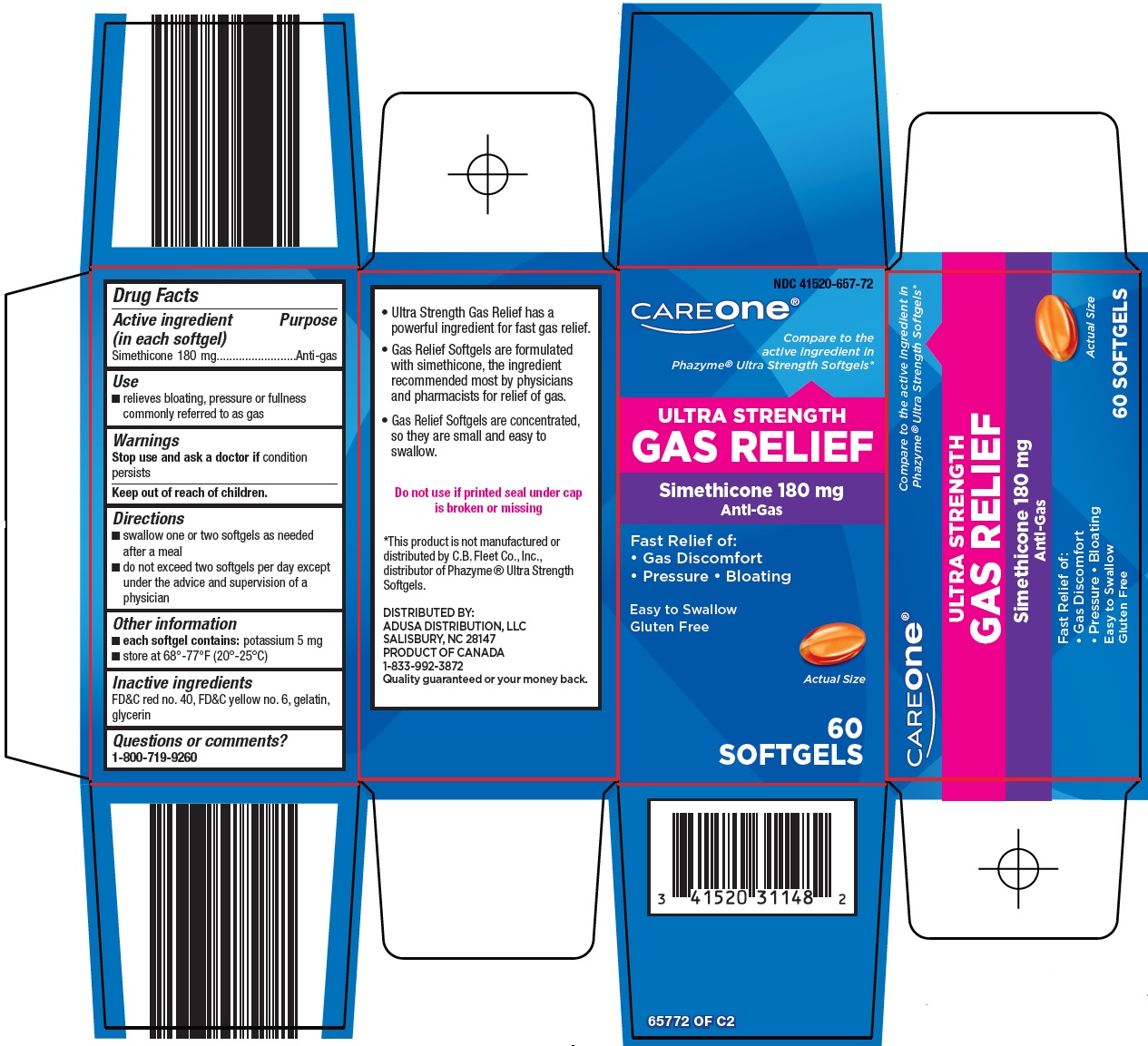 DRUG LABEL: Care One Gas Relief
NDC: 41520-657 | Form: CAPSULE, LIQUID FILLED
Manufacturer: American Sales Company
Category: otc | Type: HUMAN OTC DRUG LABEL
Date: 20240915

ACTIVE INGREDIENTS: DIMETHICONE 180 mg/1 1
INACTIVE INGREDIENTS: SILICON DIOXIDE; FD&C RED NO. 40; FD&C YELLOW NO. 6; GELATIN, UNSPECIFIED; GLYCERIN

American Sales Company Gas Relief Drug Facts

Active ingredient (in each softgel)

Simethicone 180 mg

Purpose

Anti-gas

Use

- relieves bloating, pressure or fullness commonly referred to as gas

Warnings

Stop use and ask a doctor if

condition persists

Directions

- swallow one or two softgels as needed after a meal
- do not exceed two softgels per day except under the advice and supervision of a physician

Other information

- each softgel contains: potassium 5 mg
- store at 68°-77°F (20°-25°C)

Inactive ingredients

FD&C red no. 40, FD&C yellow no. 6, gelatin, glycerin

Questions or comments?

1-800-719-9260

Principal Display Panel

CAREone®

Compare to the active ingredient in Phazyme® Ultra Strength Softgels

ULTRA STRENGTH

GAS RELIEF

Simethicone 180 mg

Anti-Gas

Fast Relief of:

● Gas Discomfort

● Pressure

● Bloating

Easy to Swallow

Gluten Free

Actual Size

60 SOFTGELS